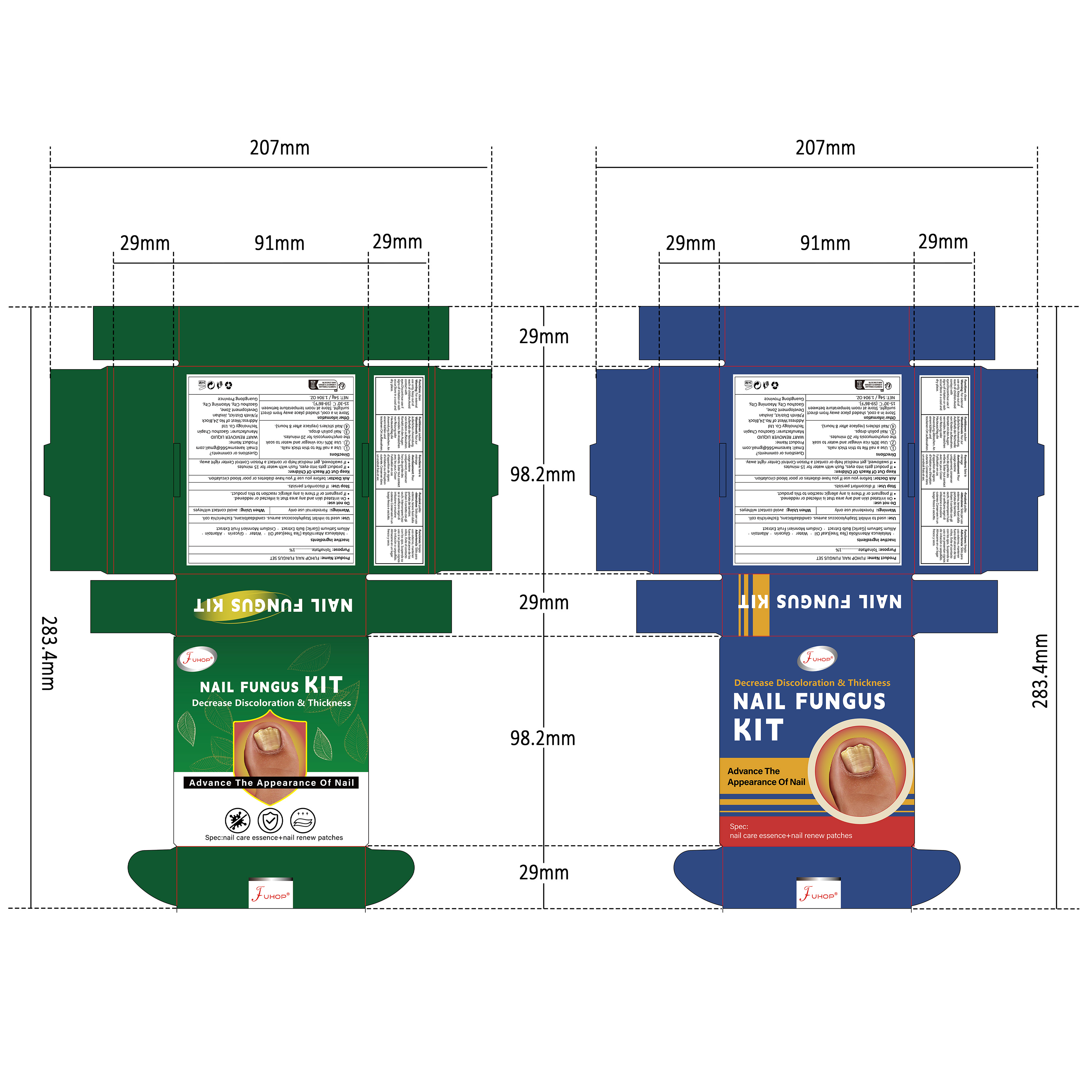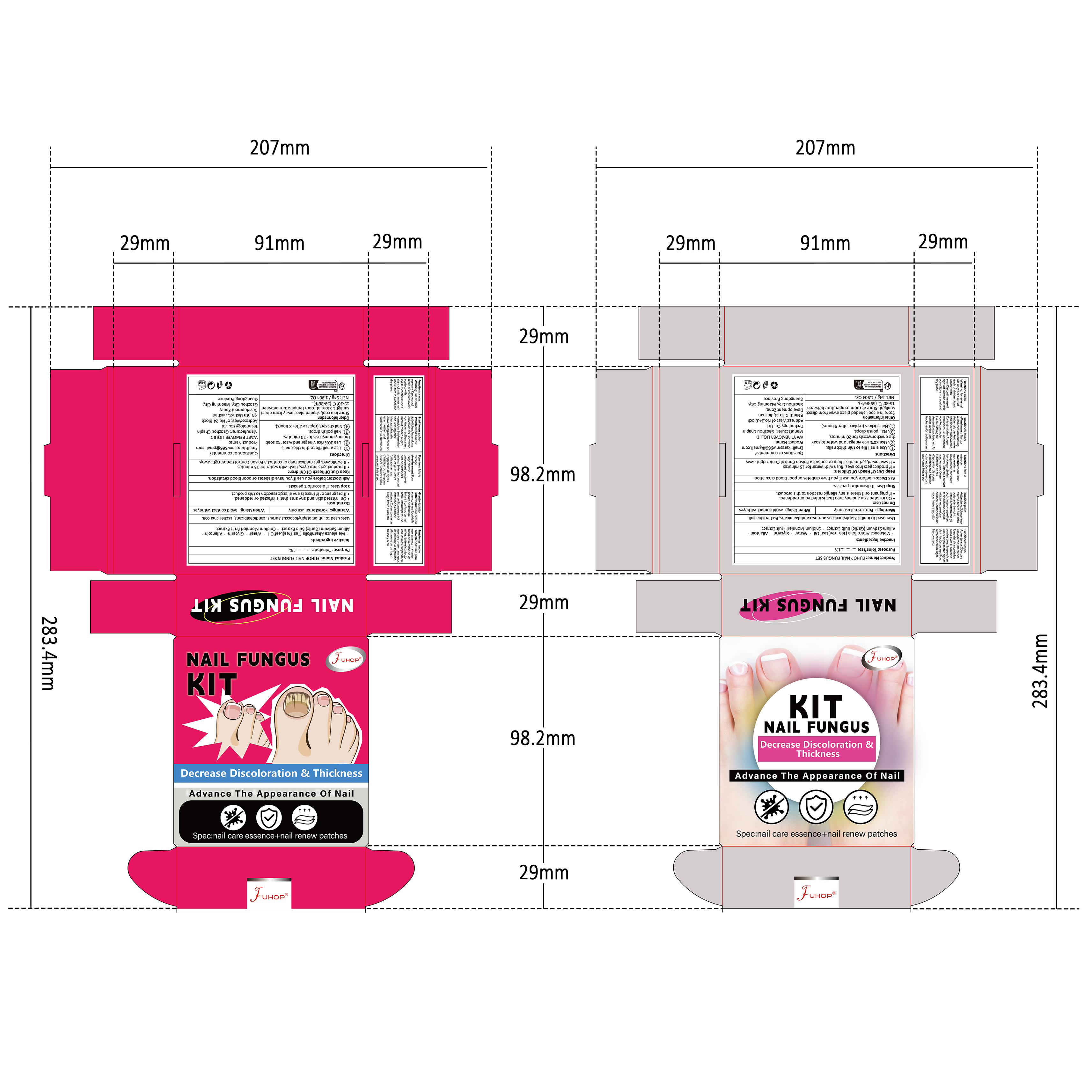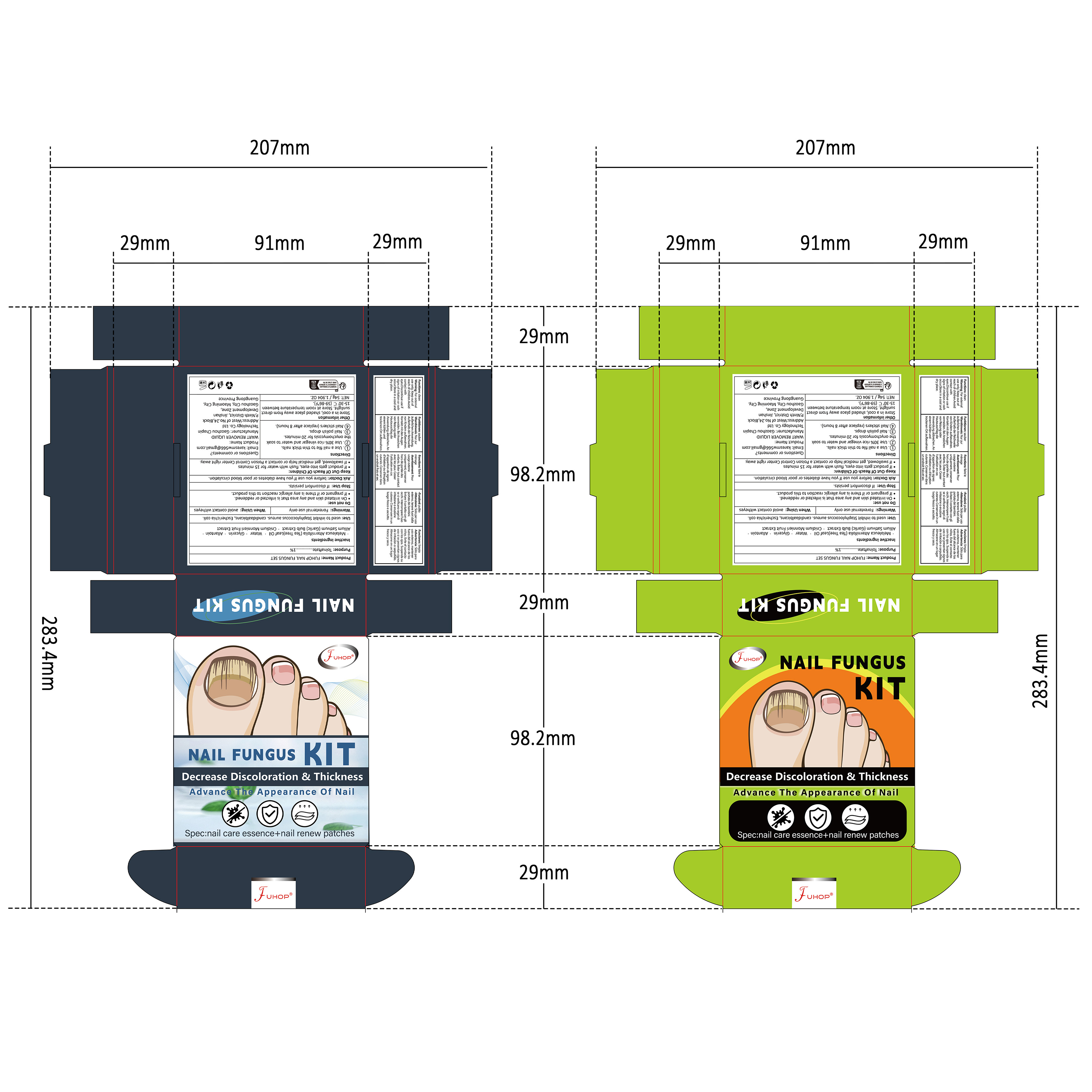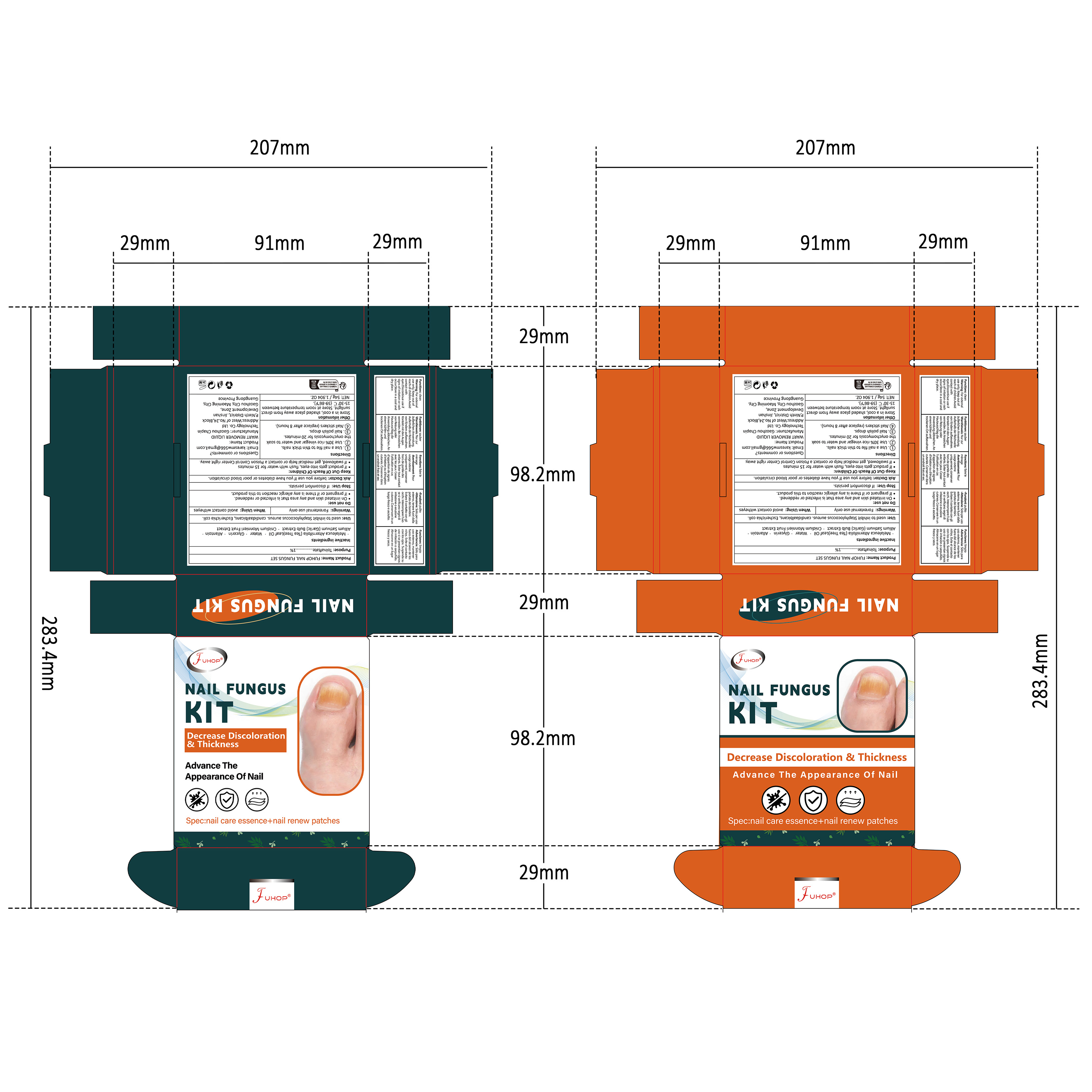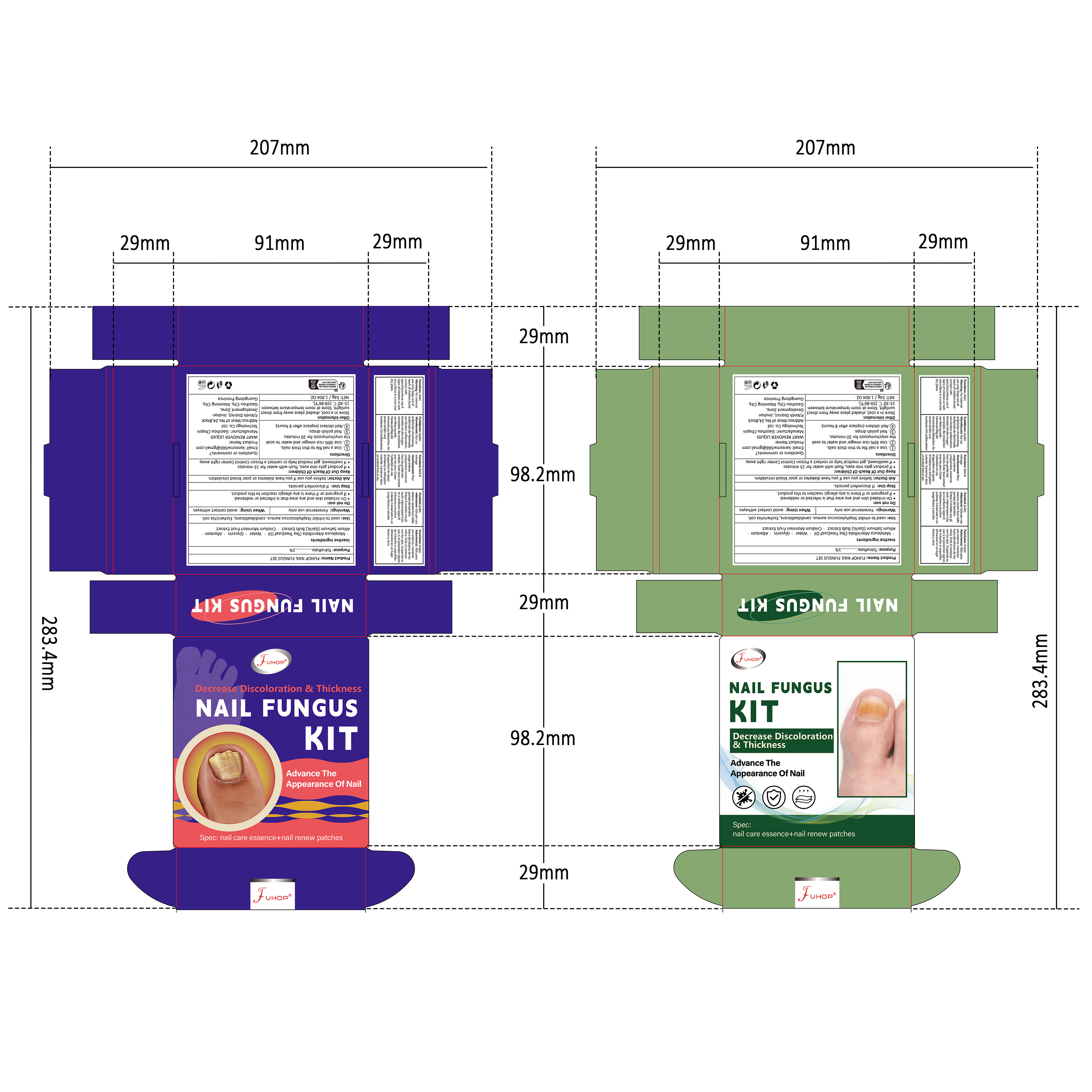 DRUG LABEL: FUHOP NAIL FUNGUS SET
NDC: 84168-049 | Form: LIQUID
Manufacturer: Gaozhou Chapin Technology Co., Ltd
Category: otc | Type: HUMAN OTC DRUG LABEL
Date: 20240930

ACTIVE INGREDIENTS: TOLNAFTATE 1 g/100 g
INACTIVE INGREDIENTS: GARLIC; MELALEUCA ALTERNIFOLIA (TEA TREE) LEAF OIL; WATER; ALLANTOIN; GLYCERIN; CNIDIUM MONNIERI FRUIT

Active ingredients

Tolnaftate 1%

Purpose

Anti-fungal

Use

Proven effective in the treatment of most athlete’s foot (tinea pedis)and ringworm(tinea corporis).

Warnings

For external use only

Do not use

■On irritated skin and any area that is infected or reddened.
■If pregnant or if there is any allergic reaction to this product.

When Using

avoid contact witheyes

Stop Use

If discomfort persists.

Ask Doctor

before you use If you have diabetes or poor blood circulation.

Keep Out Of Reach Of Children

■If product gets into eyes, flush with water for 15 minutes
■If swallowed, get medical help or contact a Poison Control Center right away.

Inactive ingredients

Melaleuca Alternifolia (Tea Tree)Leaf Oil , Water ,Glycerin , Allantoin,Allium Sativum (Garlic) Bulb Extract ，Cnidium Monnieri Fruit Extract ，Trimethoxysilylpropyl Steardimonium Chloride

DOSAGE & ADMINISTRATION SECTION

One patch per day, each patch contains 1 mg of tolnaftate